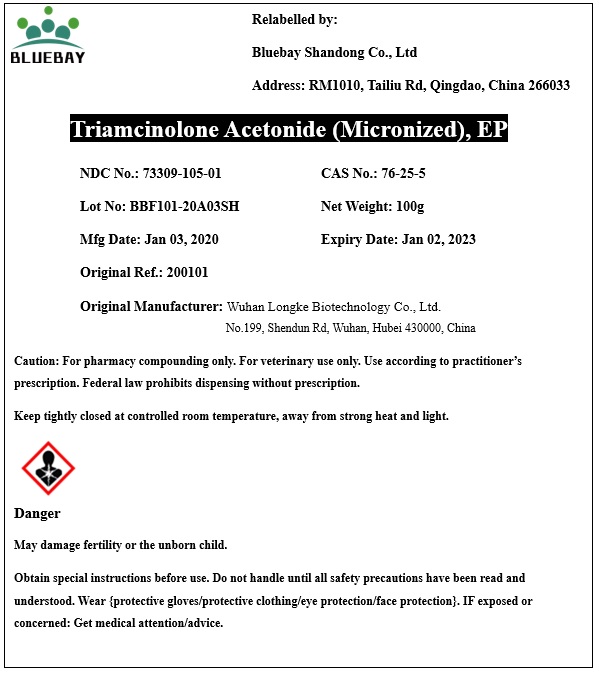 DRUG LABEL: Triamcinolone acetonide
NDC: 73309-105 | Form: POWDER
Manufacturer: BLUEBAY SHANDONG CO.,LTD
Category: other | Type: BULK INGREDIENT
Date: 20200323

ACTIVE INGREDIENTS: TRIAMCINOLONE ACETONIDE 1 g/1 g

Triamcinolone acetonide Micronized